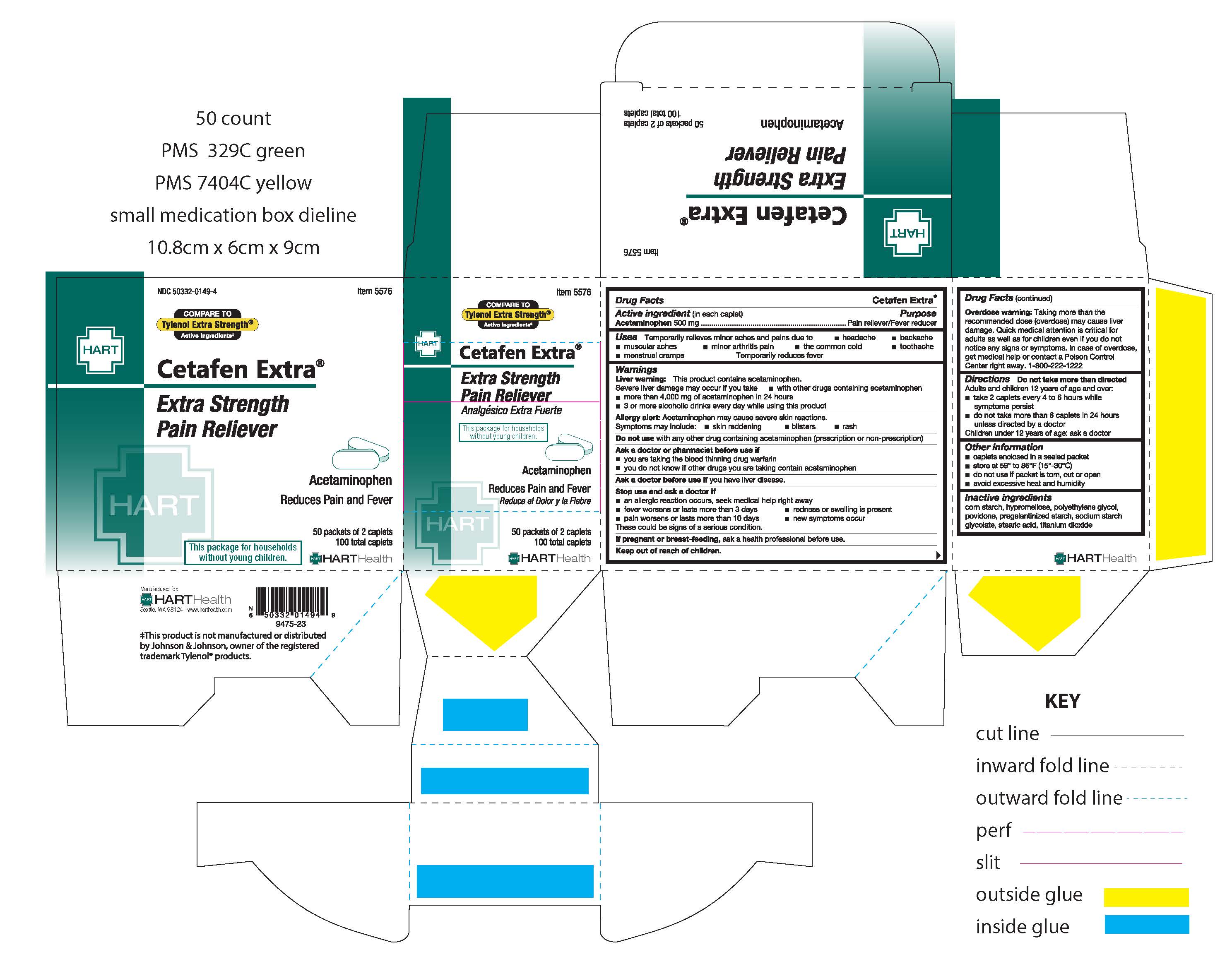 DRUG LABEL: CETAFEN EXTRA
NDC: 50332-0149 | Form: TABLET
Manufacturer: HART Health
Category: otc | Type: HUMAN OTC DRUG LABEL
Date: 20251224

ACTIVE INGREDIENTS: ACETAMINOPHEN 500 mg/1 1
INACTIVE INGREDIENTS: HYPROMELLOSES; POLYETHYLENE GLYCOL, UNSPECIFIED; STARCH, CORN; STEARIC ACID; TITANIUM DIOXIDE; POVIDONE, UNSPECIFIED

CETAFEN EXTRA

Active Ingredient (in each caplet): Acetaminophen 500mg

Purpose

Pain Reliever / Fever Reducer

Uses:

Temporarily relieves minor aches and pains due to:

- headache
- muscular aches
- backache
- minor arthritis pain
- the common cold
- toothache
- menstrual cramps

Temporarily reduces fever

Warnings:

Liver warning: This product contains acetaminophen. Severe liver damage may occur if you take:

- more than 4,000 mg of acetaminophen in 24 hours
- with other drugs containing acetaminophen
- 3 or more alcoholic drinks every day while using this product

Allergy alert: Acetaminophen may cause severe skin reactions. Symptoms may include:

- skin reddening
- rash
- blisters

Do not use with any other drug containing acetaminophen (prescription or non-prescription)

Ask a doctor or pharmacist before use if

- you are taking the blood thinning drug warfarin
- you do not know if other drugs you are taking contain acetaminophen

Ask a doctor before use if you have liver disease

Stop use and ask a doctor if

- an allergic reaction occurs, seek medical help right away
- new symptms occur
- redness or swelling is present
- fever worsens or lasts more than 3 days
- pain worsens or lasts more than 10 days

These could be signs of a serious condition

PREGNANCY OR BREAST FEEDING

If pregnant or breast-feeding, ask a health professional before use

Keep out of reach of children.

OVERDOSAGE

Overdose warning: Taking more than the recommended dose (overdose) may cause liver damage. Quick medical attention is critical for adults as well as for children even if you do not notice any signs or symptoms. In case of overdose, get medical help or contact a Poison Control Center right away. 1-800-222-1222.

Directions:

Do not take more than directed

Adults and children 12 years of age and over:

- take 2 caplets every 4 to 6 hours while symptoms persist
- do not take more than 8 caplets in 24 hours unless directed by a doctor

Children under 12 years of age: ask a doctor

Other information:

- caplets enclosed in a sealed packet
- do not use if packet is torn, cut or open
- store at 59° to 86°F (15°-30°C)
- avoid excessive heat and humidity

INACTIVE INGREDIENT

Inactive Ingredients: corn starch, hypromellose, polyethylene glycol, povidone, pregelantized starch, sodium starch glycolate, stearic acid, titanium dioxide